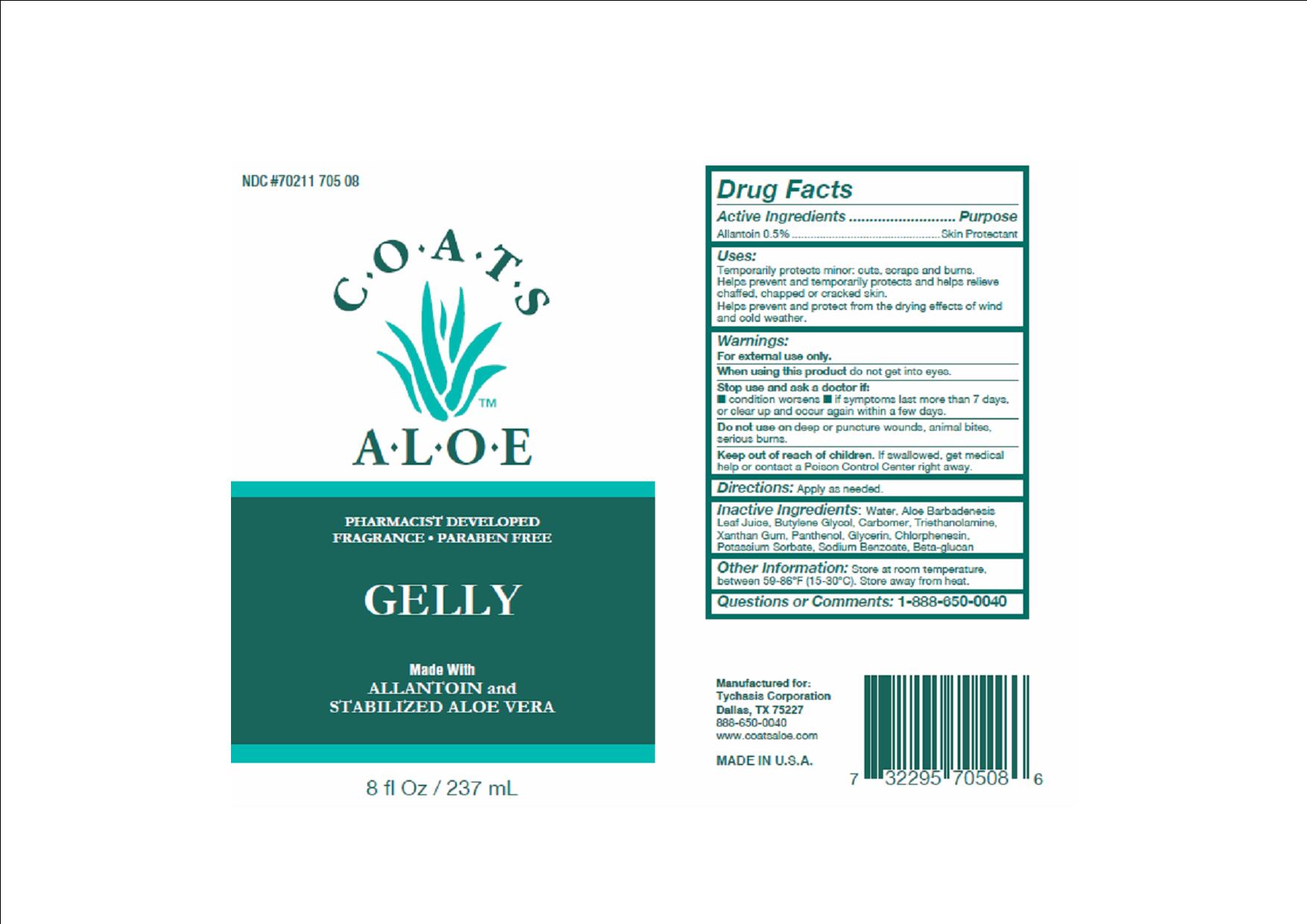 DRUG LABEL: COATS ALOE
NDC: 70211-705 | Form: JELLY
Manufacturer: TYCHASIS CORPORATION
Category: otc | Type: HUMAN OTC DRUG LABEL
Date: 20241028

ACTIVE INGREDIENTS: ALLANTOIN 0.5 g/100 mL
INACTIVE INGREDIENTS: GLYCERIN; BUTYLENE GLYCOL; XANTHAN GUM; ALOE VERA LEAF; PANTHENOL; SODIUM BENZOATE; POTASSIUM SORBATE; CHLORPHENESIN

COATS ALOE GELLY

Active Ingredient:

Allantoin 0.5%

Purpose:

Skin Protectant

Warnings:

For external use only.

Do not get into eyes.

Stop use if:

Stop use and ask a doctor if condition worsens, symptoms last more than 7 days, or clear up and occur again within a few days.

Uses:

Temporarily protects minor:

- cuts
- scrapes
- burns

Helps prevent and temporarily protects and helps relieve chaffed, chapped or cracked skin.

Helps prevent and protect from the drying effects of wind and cold weather.

Caution:

Do not use on deep puncture wounds, animals bites, serious burns.

Keep out of reach of children:

If swallowed, get medical help or contact a poison control center right away.

Directions:

Apply as needed.

Inactive Ingredients:

aloe barbadenesis leaf juice, water, butylene glycol, carbomer, triethanolamine, xanthun gum, panthenol, glycerin, chlorphenesin, potassium sorbate, sodium benzoate, beta-glucan

Questions:

Toll free 888-650-0040